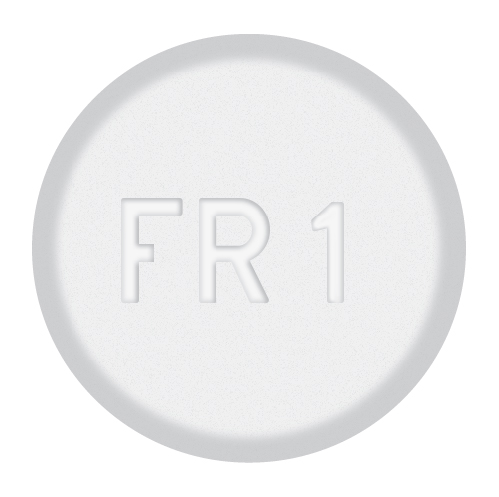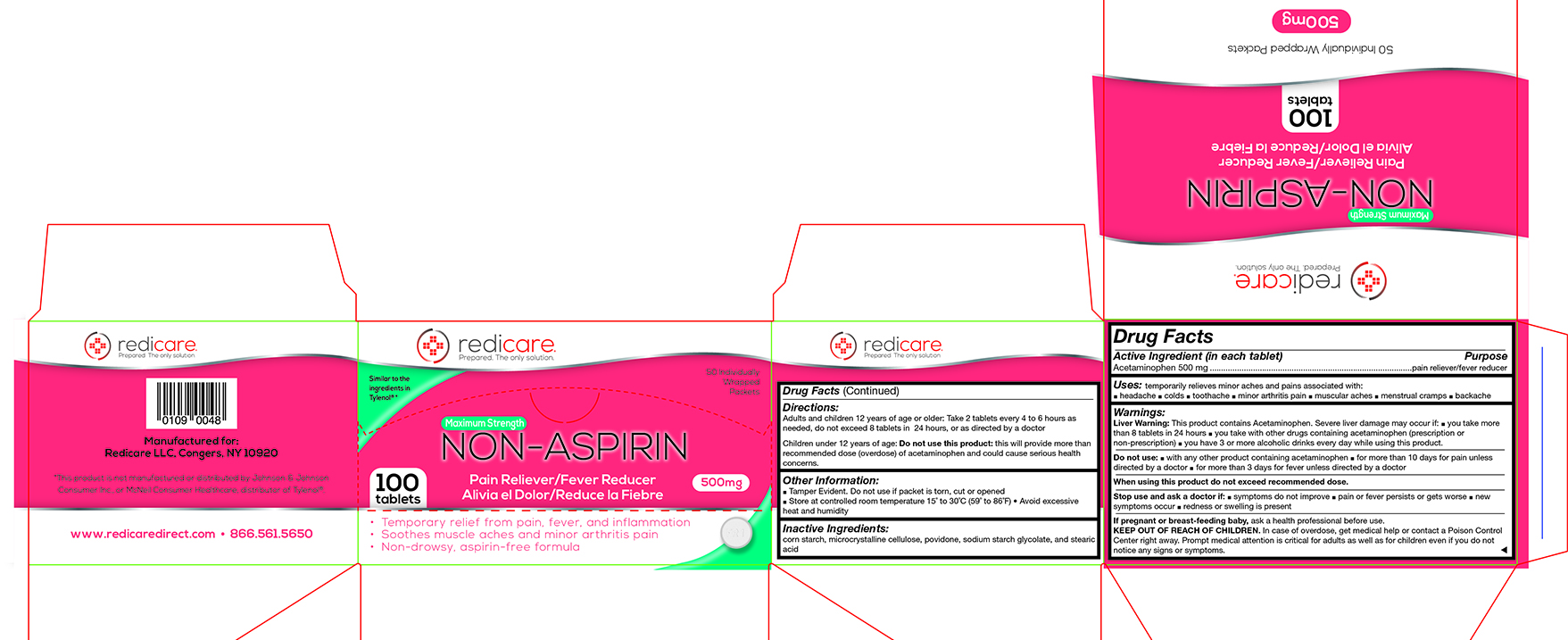 DRUG LABEL: Non-Aspirin Acetaminophen
NDC: 71105-210 | Form: TABLET
Manufacturer: Redicare LLC
Category: otc | Type: HUMAN OTC DRUG LABEL
Date: 20210702

ACTIVE INGREDIENTS: ACETAMINOPHEN 500 mg/1 1
INACTIVE INGREDIENTS: STARCH, CORN; CELLULOSE, MICROCRYSTALLINE; POVIDONE; SODIUM STARCH GLYCOLATE TYPE A CORN; STEARIC ACID

Acetaminophen (non-aspirin)

Active Ingredient (in each tablet) ..................................................... Purpose

Acetaminophen 500 mg .....................................................................................pain reliever/fever reducer

Uses:

temporarily relieves minor aches and pains associated with ■ a headache ■ colds ■ a toothache ■ minor arthritis pain ■ muscular aches ■ menstrual cramps ■ a backache

Warnings:

Liver Warning: This product contains Acetaminophen. Severe liver damage may occur if: ■ you take more than 8 tablets in 24 hours ■ you take with other drugs containing acetaminophen (prescription or non-prescription) ■ you have 3 or more alcoholic drinks every day while using this product.

Do not use:

■ with any other product containing acetaminophen ■ for more than 10 days for pain unless directed by a doctor ■ for more than 3 days for fever unless directed by a doctor

Stop use and ask a doctor if

■ symptoms do not improve ■ pain or fever persists or gets worse ■ new symptoms occur ■ redness or swelling is present

If pregnant or breast-feeding a baby,

ask a health professional before use.

KEEP OUT OF REACH OF CHILDREN.

In a case of overdose, get medical help or contact a Poison Control Center right away. Prompt medical attention is critical for adults as well as for children even if you do not notice any signs or symptoms.

Directions:

Adults and children 12 years of age or older: Take 2 tablets every 4 to 6 hours as needed, do not exceed 8 tablets in 24 hours, or as directed by a doctor
Children under 12 years of age: Do not use this product: this will provide more than the recommended dose (overdose) of acetaminophen and could cause serious health concerns.

Other Information:

■ Tamper Evident. Do not use if packet is torn, cut or opened ■ Store at controlled room temperature 15˚ to 30˚C (59˚ to 86˚F) • Avoid excessive heat and humidity

Inactive Ingredients:

corn starch, microcrystalline cellulose, povidone, sodium starch glycolate, and stearic acid